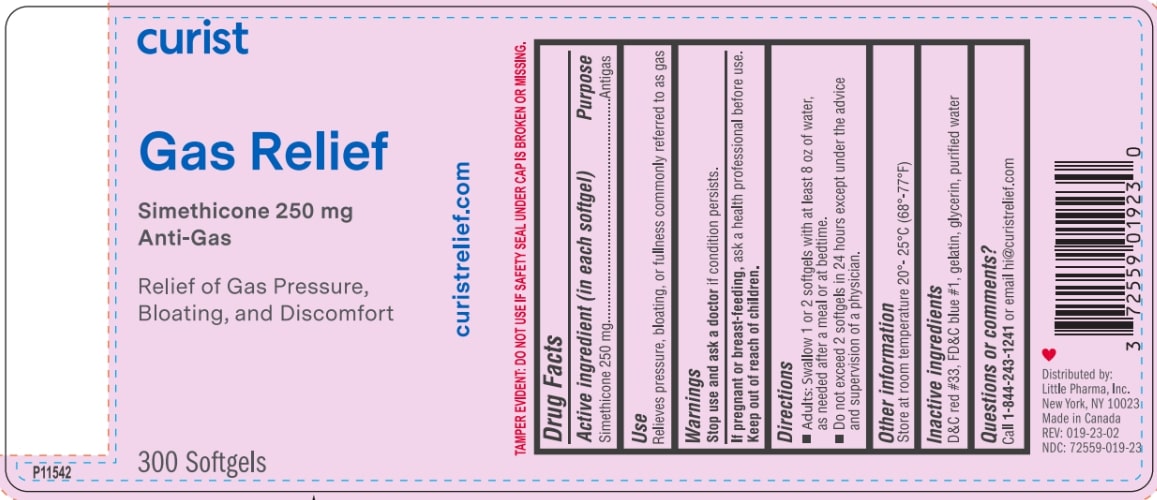 DRUG LABEL: Curist Gas Relief
NDC: 72559-019 | Form: CAPSULE, LIQUID FILLED
Manufacturer: Little Pharma, Inc.
Category: otc | Type: HUMAN OTC DRUG LABEL
Date: 20250204

ACTIVE INGREDIENTS: DIMETHICONE 250 mg/1 1
INACTIVE INGREDIENTS: GELATIN, UNSPECIFIED; GLYCERIN; WATER; FD&C BLUE NO. 1; D&C RED NO. 33

Curist Gas Relief Maximum Strength (Simethicone)

Drug Facts

Active ingredient (in each softgel)

Simethicone 250 mg

Purpose

Antigas

Warnings

Stop use and ask doctor if condition persists

PREGNANCY OR BREAST FEEDING

If pregnant or breast feeding, ask a health professional before use.

Keep out of reach of children.

Use

Relieves pressure, bloating, or fullness commonly referred to as gas

Directions

- Adults: Swallow 1 or 2 softgels with at least 8 oz of water, as needed after a meal or at bedtime.
- Do not exceed 2 softgels in 24 hours except under the advice and supervision of a physician.

Other information

Store at room temperature 20-25°C (68-77°F)

INACTIVE INGREDIENT

Inactive ingredients D&C red #33, FD&C blue #1, gelatin, glycerin, and purified water

Questions or comments? 1-844-243-1241 Monday - Friday 9AM - 5PM EST

Distributed by:
Little Pharma, Inc.
New York, NY 10023

Made in Canada

PACKAGE LABEL

curist

Gas Relief Maximum Strength

Simethicone 250 mg

Anti-Gas

Fast Relief of Gas Pressure, Bloating, and Discomfort

300 Softgels